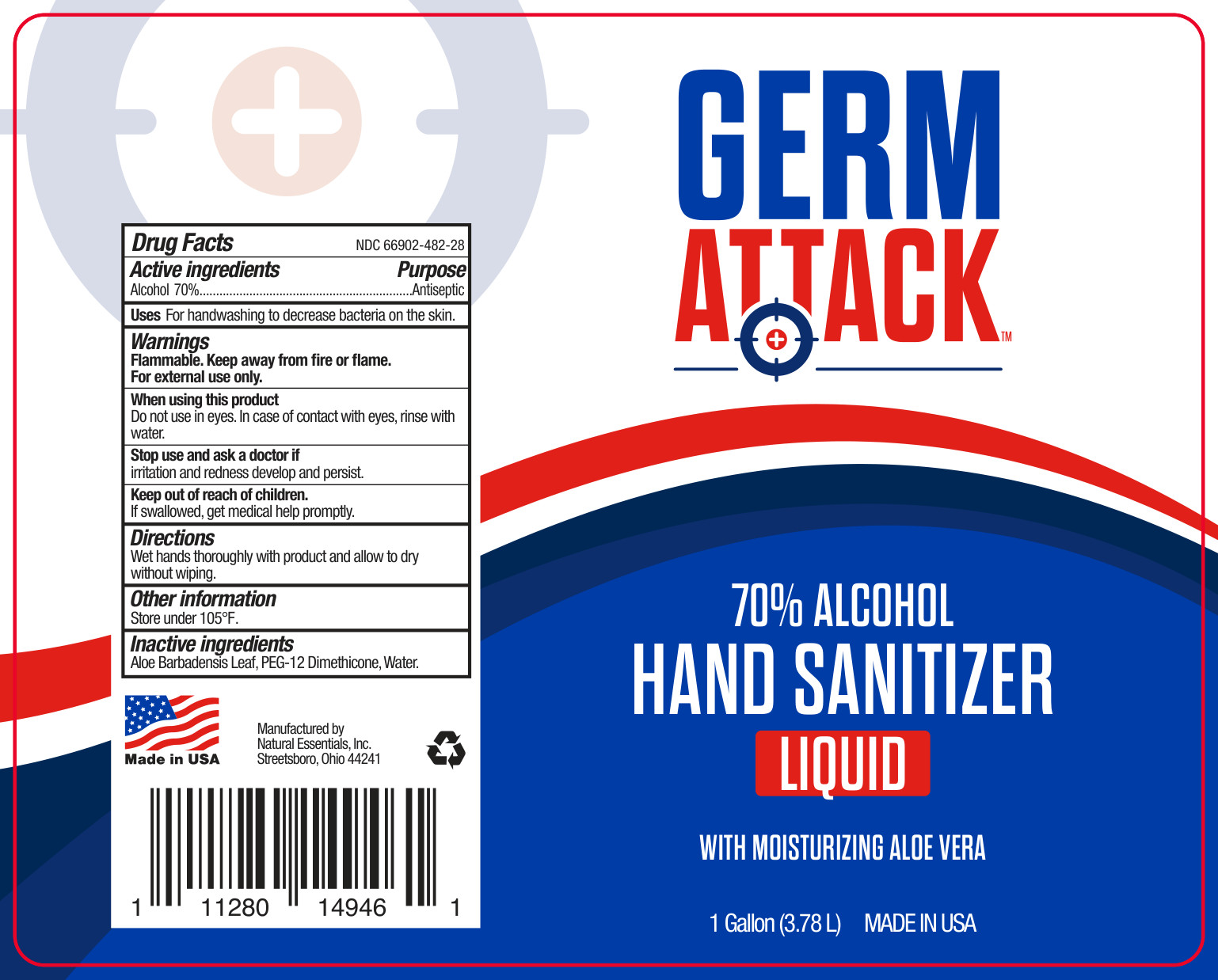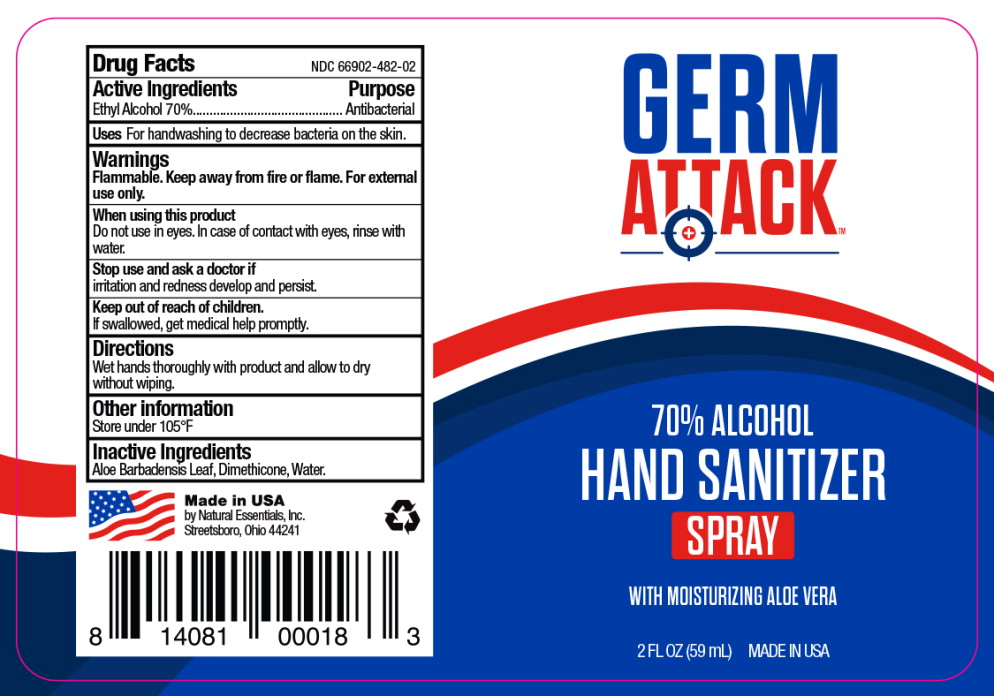 DRUG LABEL: Germ Attack Hand Sanitizer
NDC: 66902-482 | Form: LIQUID
Manufacturer: Natural Essentials, Inc.
Category: otc | Type: HUMAN OTC DRUG LABEL
Date: 20251027

ACTIVE INGREDIENTS: ALCOHOL 0.7 mL/1 mL
INACTIVE INGREDIENTS: ALOE VERA LEAF; PEG-12 DIMETHICONE; WATER

Germ Attack 70% Hand Sanitizer Liquid

Drug Facts

Active Ingredients

Alcohol 70%

Purpose

Antiseptic

Uses

For handwashing to decrease bacteria on the skin.

Warnings

Flammable. Keep away from fire or flame. For external use only.

When using this product

Do not use in eyes. In case of contact with eyes, rinse with water.

Stop use and ask a doctor if

irritation and redness develop and persist.

Keep out of reach of children.

If swallowed, get medical help promptly.

Directions

Wet hands thoroughly with product and allow to dry without wiping.

Other information

Store under 105°F

Inactive Ingredients

Aloe Barbadensis Leaf, PEG-12 Dimethicone, Water

Principal Display Panel – Jug Label

GERM
ATTACK ™

70% ALCOHOL

HAND SANITIZER

LIQUID

WITH MOISTURIZING ALOE VERA

1 gallon (3.78 L) MADE IN USA

Principal Display Panel – Spray Label

GERM
ATTACK ™

70% ALCOHOL

HAND SANITIZER

SPRAY

WITH MOISTURIZING ALOE VERA

2 FL OZ (59 mL) MADE IN USA